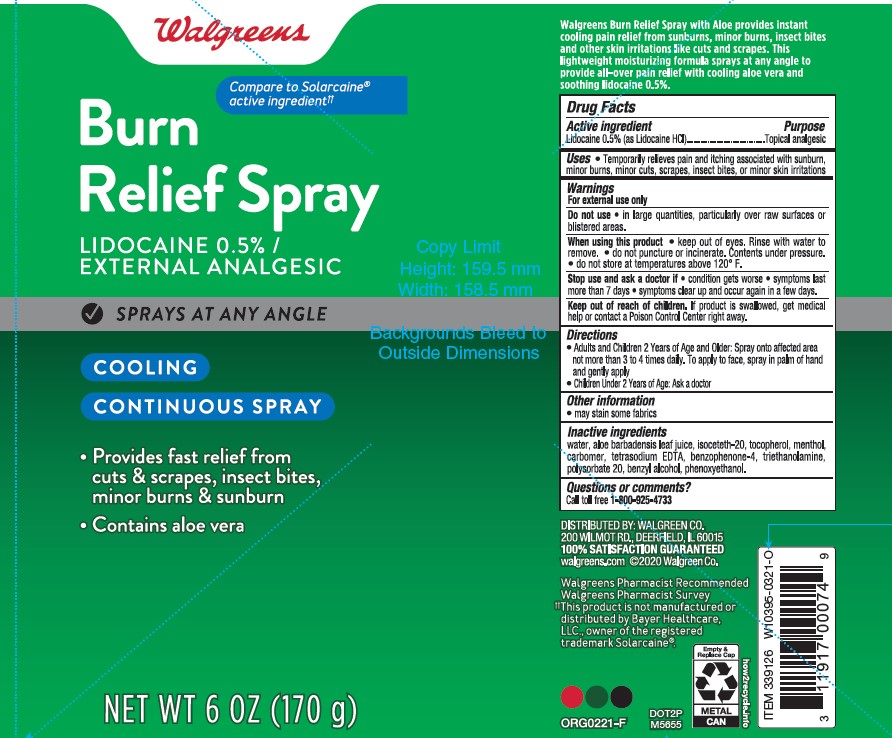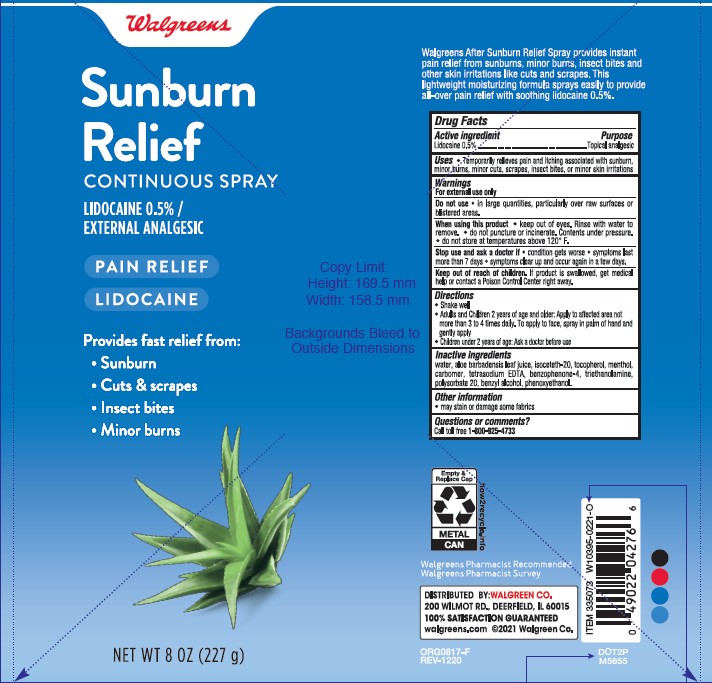 DRUG LABEL: Walgreens Sunburn Relief
NDC: 0363-0978 | Form: SPRAY
Manufacturer: WALGREEN COMPANY
Category: otc | Type: HUMAN OTC DRUG LABEL
Date: 20241014

ACTIVE INGREDIENTS: LIDOCAINE HYDROCHLORIDE 5 mg/1 g
INACTIVE INGREDIENTS: LEVOMENTHOL; BENZYL ALCOHOL; PHENOXYETHANOL; WATER; POLYSORBATE 20; .ALPHA.-TOCOPHEROL, DL-; ALOE VERA LEAF; ISOCETETH-20; TROLAMINE; CARBOMER HOMOPOLYMER TYPE C (ALLYL PENTAERYTHRITOL CROSSLINKED); EDETATE SODIUM; SULISOBENZONE

Walgreens Sunburn Relief Continuous Spray

Active Ingredients

Lidocaine 0.5% (as Lidocaine HCl)

Purpose

Topical Analgesic

Uses

Temporary relieves pain and itching associated with sunburn, minor burns, minor cuts, scrapes, insect bites, or , minor skin irritations

Warnings

For external use only

Do not use

- in large quantities, particularly over raw surfaces or blistered areas

When using this product

- keep out of eyes. Rinse with water to remove.
- do not puncture or incinerate. Contents under pressure.
- do not store at temperatures above 120°F.

Stop use and ask a doctor if

- condition gets worse
- symptoms last more than 7 days
- symptoms clear up and occur again in a few days

Keep out of reach of children

If product is swallowed, get medical help or contact a Poison Control Center right away.

Directions

- Adults and Children 2 Years of Age andAolder; Spray onto affected area not more than 3 to 4 times daily. To apply to face, spray in palm of hand and gently apply.
- Children Under 2 Years of Age: Ask a doctor.

Other information

- may stain some fabrics

Inactive Ingredients

Water, Aloe Barbadensis Leaf Juice, Isoceteth-20, Tocophorol, Menthol, Carbomer, Tetrasodium EDTA, Benzophenone 4, Triethanolamine, Polysorbate 20, Benzyl Alcohol, Phenoxyethanol